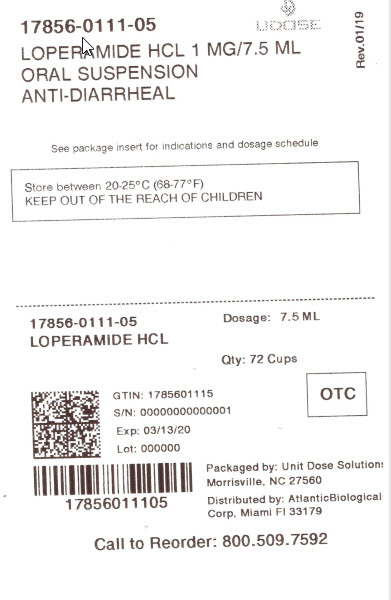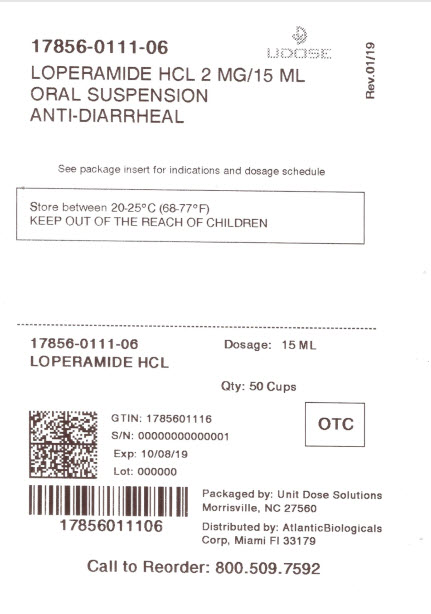 DRUG LABEL: good neighbor pharmacy Loperamide hydrochloride
NDC: 17856-0111 | Form: SUSPENSION
Manufacturer: ATLANTIC BIOLOGICALS CORP.
Category: otc | Type: HUMAN OTC DRUG LABEL
Date: 20210125

ACTIVE INGREDIENTS: LOPERAMIDE HYDROCHLORIDE 1 mg/7.5 mL
INACTIVE INGREDIENTS: ANHYDROUS CITRIC ACID; CARBOXYMETHYLCELLULOSE SODIUM; D&C YELLOW NO. 10; FD&C BLUE NO. 1; GLYCERIN; CELLULOSE, MICROCRYSTALLINE; PROPYLENE GLYCOL; WATER; SODIUM BENZOATE; SUCRALOSE; TITANIUM DIOXIDE; XANTHAN GUM

Amerisource Bergen Loperamide Hydrochloride Oral Suspension Drug Facts

Active ingredient (in each 7.5 mL)

Loperamide HCl 1 mg

Purpose

Anti-diarrheal

Use

controls symptoms of diarrhea, including Travelers’ Diarrhea

Warnings

Allergy alert: Do not use if you have ever had a rash or other allergic reaction to loperamide HCl

Do not use

if you have bloody or black stool

Ask a doctor before use if you have

- fever
- mucus in the stool
- a history of liver disease

Ask a doctor or pharmacist before use if you are

taking antibiotics

When using this product

- tiredness, drowsiness or dizziness may occur. Be careful when driving or operating machinery.

Stop use and ask a doctor if

- symptoms get worse
- diarrhea lasts for more than 2 days
- you get abdominal swelling or bulging.

These may be signs of a serious condition.

If pregnant or breast-feeding,

ask a health professional before use.

Keep out of reach of children.

In case of overdose, get medical help or contact a Poison Control Center right away. (1-800-222-1222)

Directions

- drink plenty of clear fluids to help prevent dehydration caused by diarrhea
- find right dose on chart. If possible, use weight to dose; otherwise use age.
- shake well before using
- only use attached measuring cup to dose product

adults and children; 12 years and over | 30 mL (6 tsp) after the first loose stool; 15 mL (3 tsp) after each subsequent loose stool; but no more than 60 mL (12 tsp) in 24 hours
children 9-11 years; (60-95 lbs) | 15 mL (3 tsp) after the first loose stool; 7.5 mL (1 1/2 tsp) after each subsequent loose stool; but no more than 45 mL (9 tsp) in 24 hours
children 6-8 years; (48-59 lbs) | 15 mL (3 tsp) after the first loose stool; 7.5 mL (1 1/2 tsp) after each subsequent loose stool; but no more than 30 mL (6 tsp) in 24 hours
children under; 6 years; (up to 47 lbs) | ask a doctor

Other information

- each 30 mL (6 tsp) contains: sodium 15 mg
- store between 20-25°C (68-77°F)
- see side panel for lot number and expiration date

Inactive ingredients

anhydrous citric acid, carboxymethylcellulose sodium, D&C yellow no. 10, FD&C blue no. 1, glycerin, microcrystalline cellulose, natural and artificial mint flavor, propylene glycol, purified water, simethicone, sodium benzoate, sucralose, titanium dioxide, xanthan gum

DISTRIBUTED BY: ATLANTIC BIOLOGICALS CORP. 20101 N.E 16TH PLACE MIAMI,FL 33179

1-800-719-9260

Package/Label Principal Display Panel

Compare to Imodium® A-D active ingredient

Loperamide Hydrochloride Oral Suspension

anti-diarrheal

Controls the Symptoms of Diarrhea

mint flavor

NDC 17856-0111-06